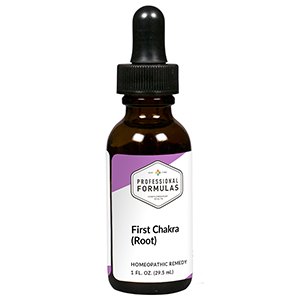 DRUG LABEL: First Chakra (Root)
NDC: 63083-7301 | Form: LIQUID
Manufacturer: Professional Complementary Health Formulas
Category: homeopathic | Type: HUMAN OTC DRUG LABEL
Date: 20190815

ACTIVE INGREDIENTS: MARSDENIA CUNDURANGO WHOLE 6 [hp_X]/29.5 mL; ARNICA MONTANA WHOLE 8 [hp_X]/29.5 mL; HELLEBORUS NIGER ROOT 8 [hp_X]/29.5 mL; POTASSIUM PHOSPHATE, UNSPECIFIED FORM 8 [hp_X]/29.5 mL; MAGNESIUM PHOSPHATE, DIBASIC TRIHYDRATE 8 [hp_X]/29.5 mL; SODIUM FLUORIDE 8 [hp_X]/29.5 mL; APIS MELLIFERA 12 [hp_X]/29.5 mL; BOS TAURUS BILE 12 [hp_X]/29.5 mL; LYCOSA TARANTULA 12 [hp_X]/29.5 mL; FERRIC OXIDE RED 30 [hp_X]/29.5 mL; SILICON DIOXIDE 30 [hp_X]/29.5 mL
INACTIVE INGREDIENTS: ALCOHOL; WATER

RCT1

ACTIVE INGREDIENTS

Condurango 6X
Arnica montana 8X
Helleborus niger 8X
Kali phosphoricum 8X
Magnesia phosphorica 8X
Natrum chloratum 8X
Apis mellifica 12X
Fel tauri 12X
Tarentula hispana 12X
Garnierite 30X, 60X, 100X
Hematite 30X, 60X, 100X
Rose quartz 30X, 60X, 100X

QUESTIONS

Professional Formulas

PO Box 2034 Lake Oswego, OR 97035

INDICATIONS

Temporarily relieves restlessness, insecurity, impatience, greediness, anger or aggression, or obsession with materialistic matters.*

PURPOSE

*Claims based on traditional homeopathic practice, not accepted medical evidence. Not FDA evaluated.

WARNINGS

In case of overdose, get medical help or contact a poison control center right away.

Keep out of the reach of children.

PREGNANCY OR BREAST FEEDING

If pregnant or breastfeeding, ask a healthcare professional before use.

DIRECTIONS

Place drops under tongue 30 minutes before/after meals. Adults and children 12 years and over: Take 5 drops up to 4 times per day for up to one month. Consult a physician for use in children under 12 years of age.

OTHER INFORMATION

Tamper resistant. If seal is broken, do not use. After opening, close container tightly and store at room temperature away from heat.

INACTIVE INGREDIENTS

20% ethanol, purified water.

LABEL

Est 1985

Professional Formulas

Complementary Health

First Chakra (Root)

Homeopathic Remedy

1 FL. OZ. (29.5 mL)